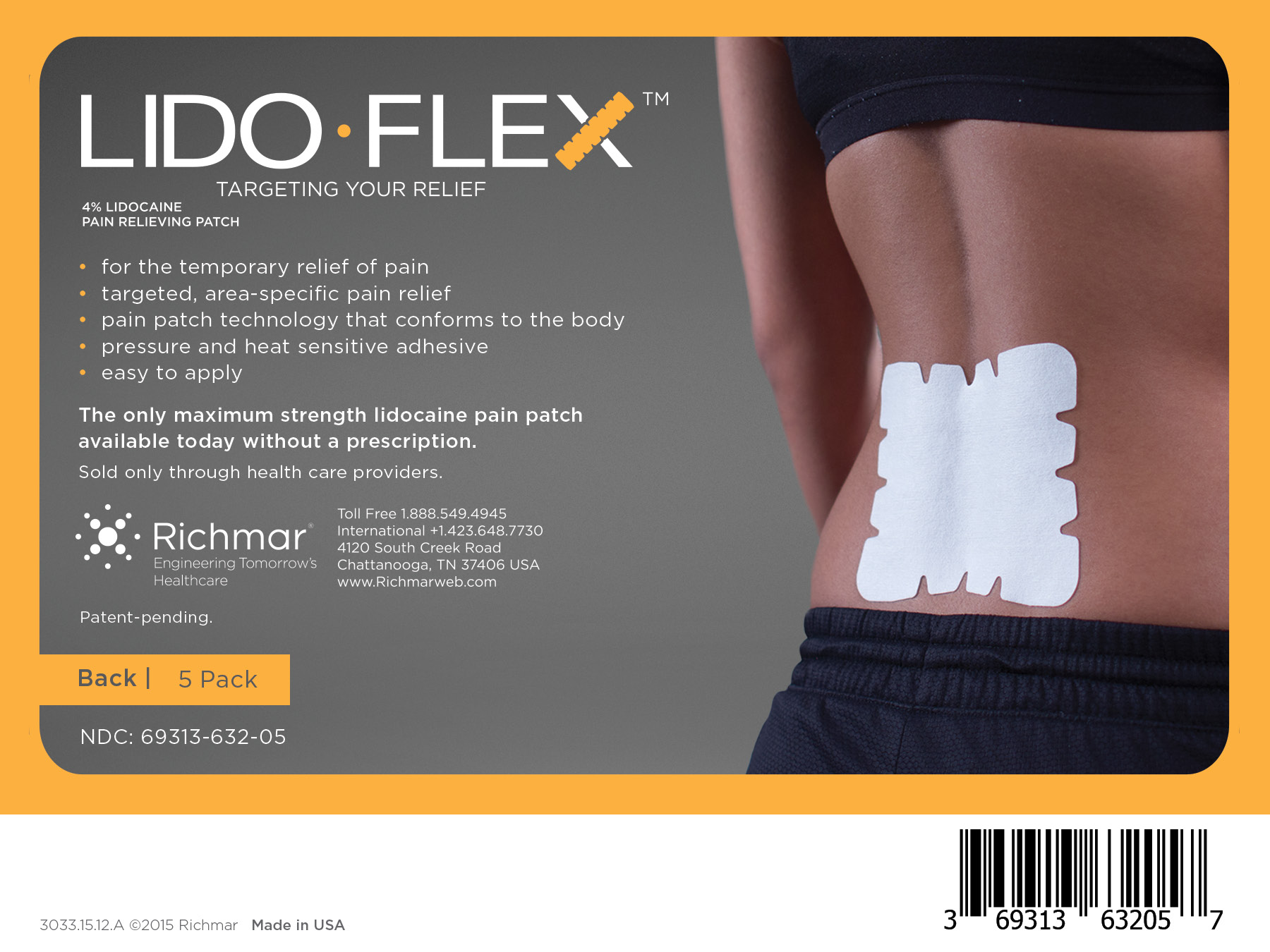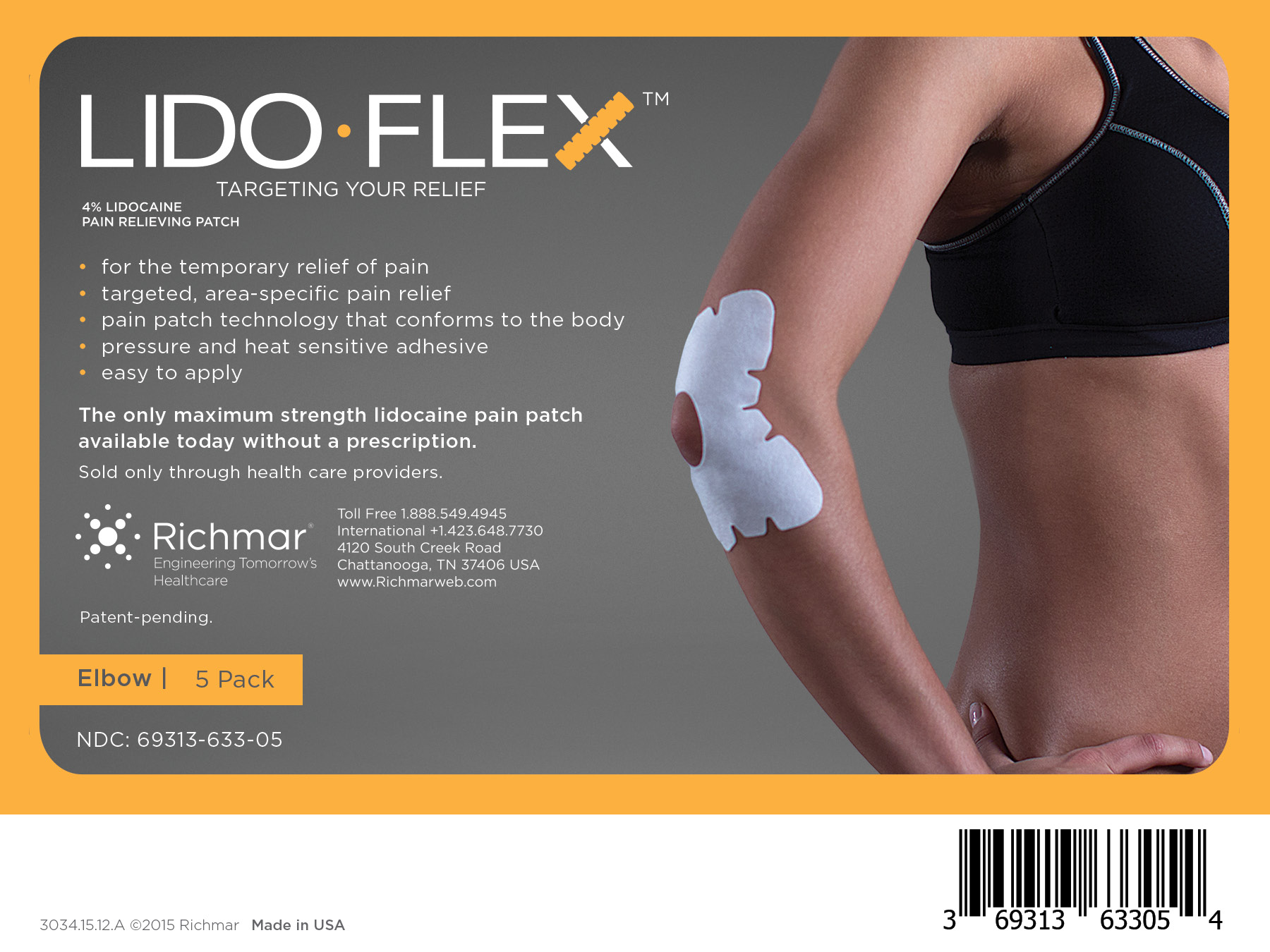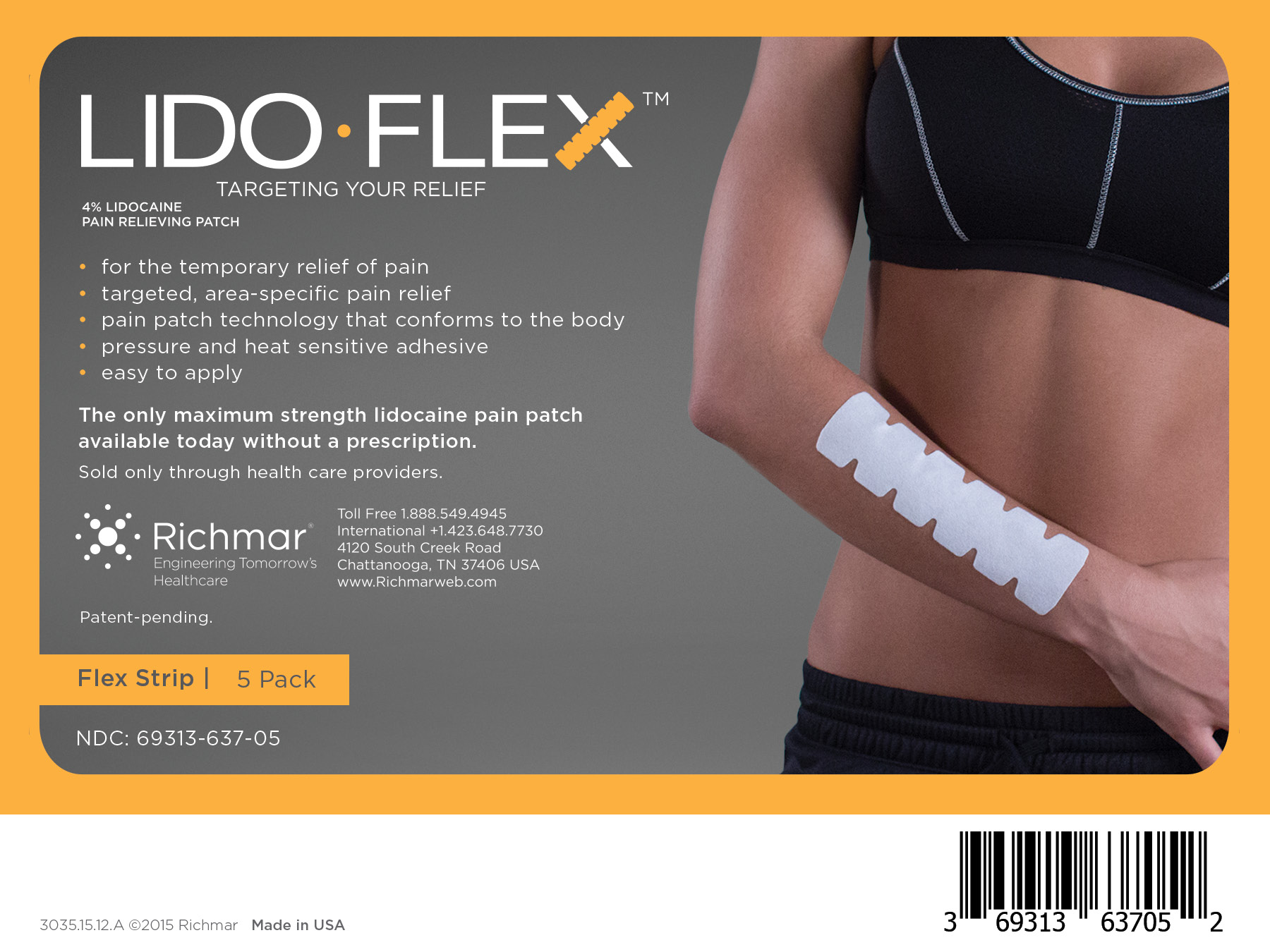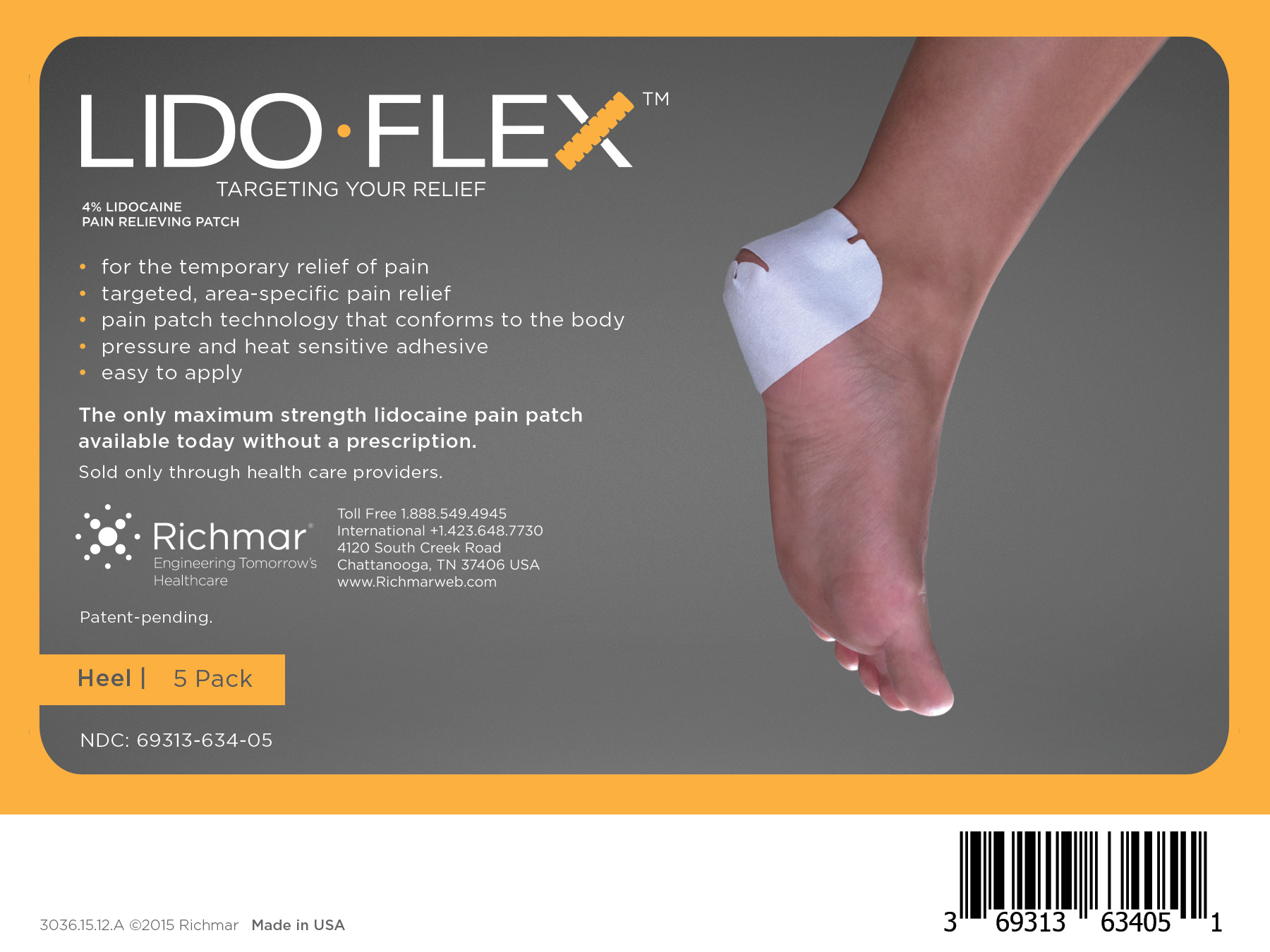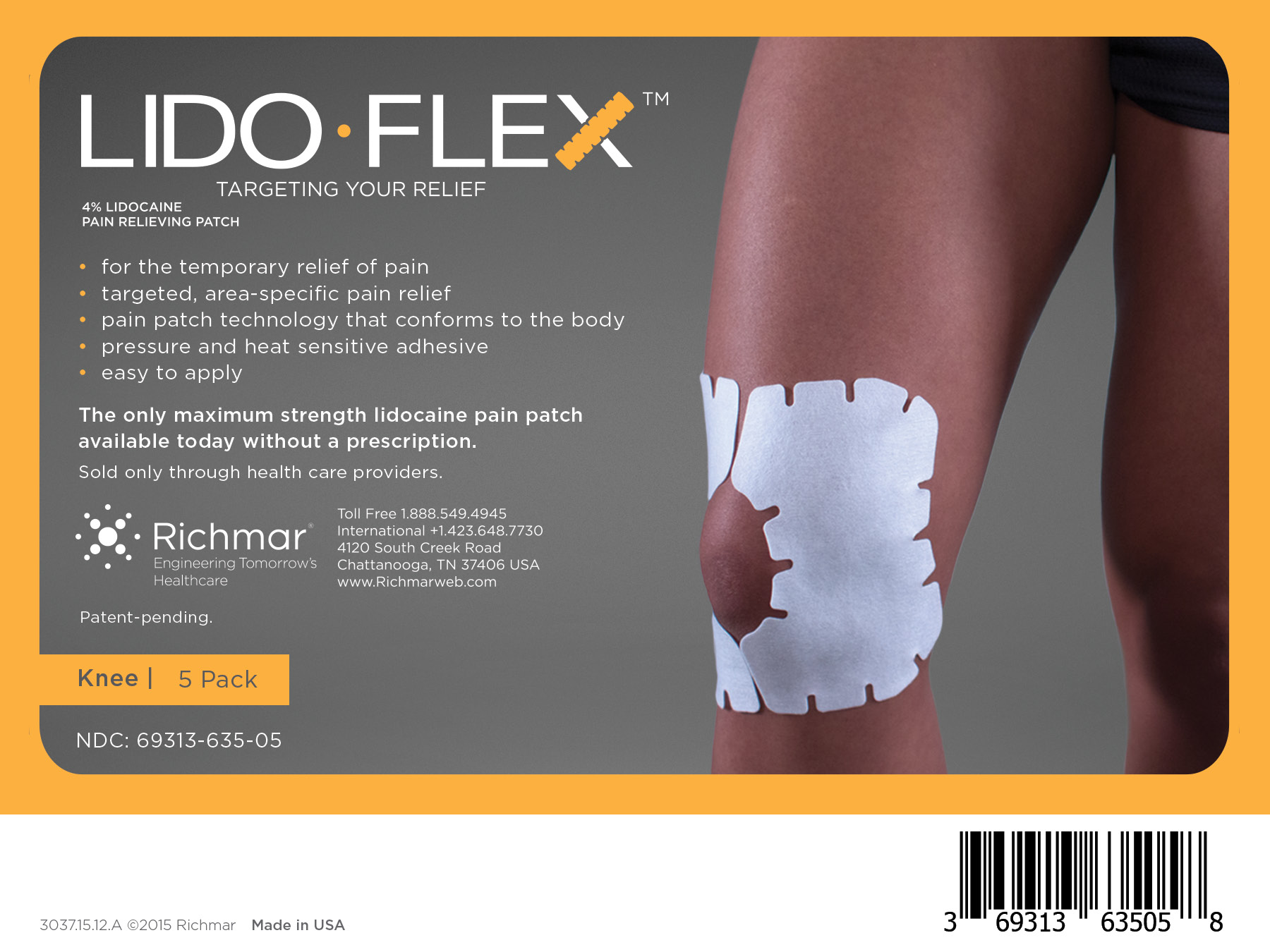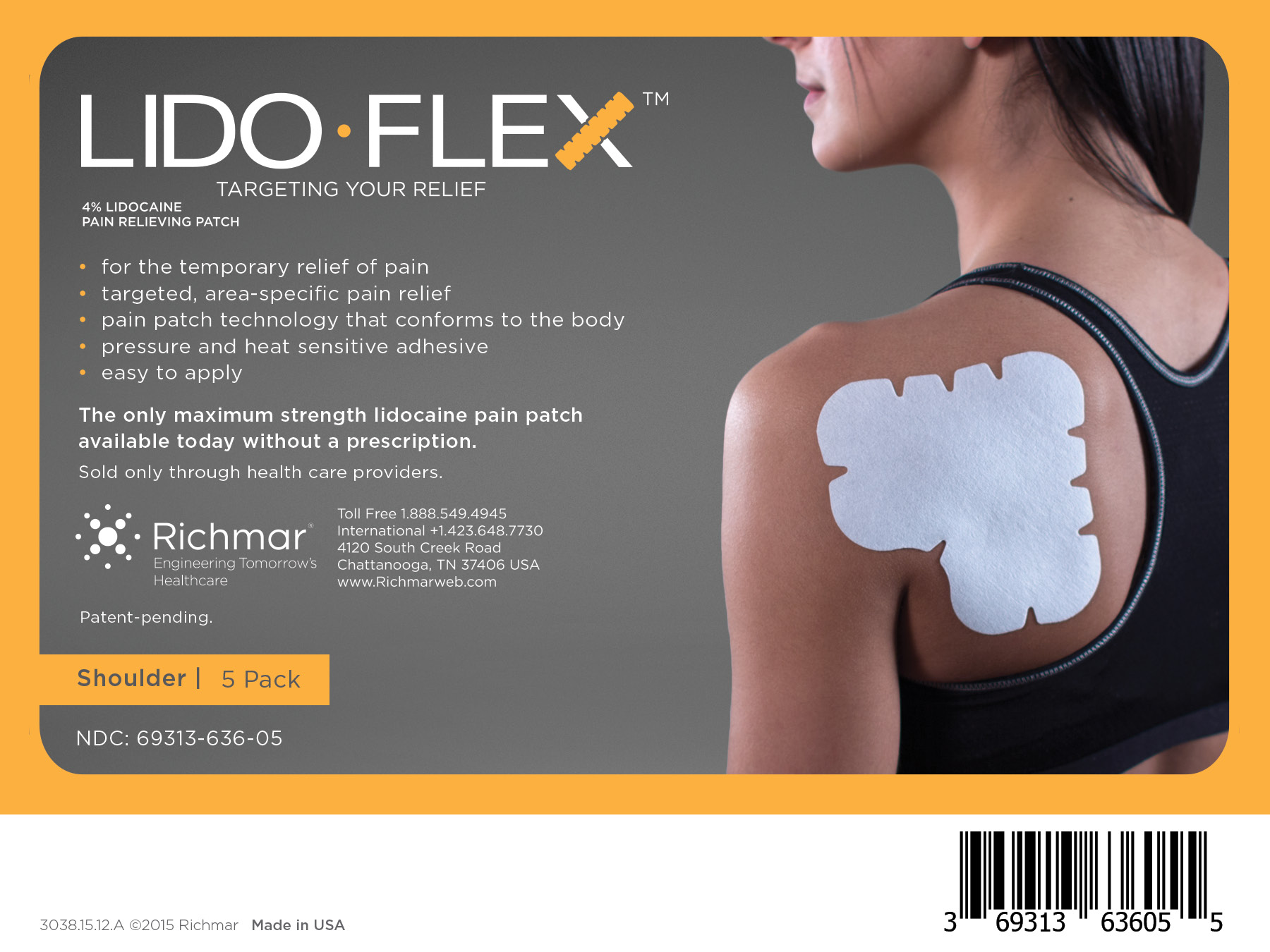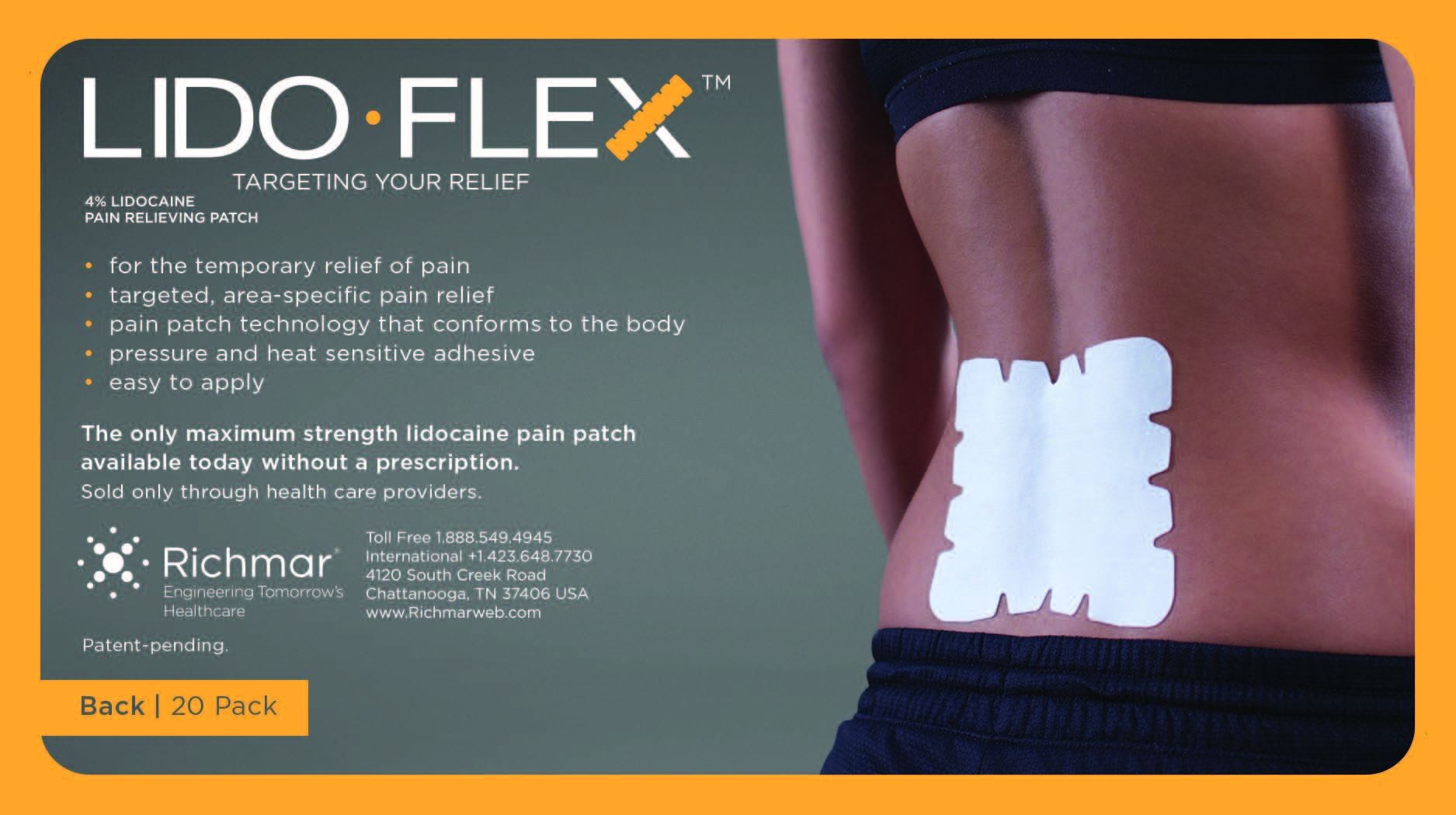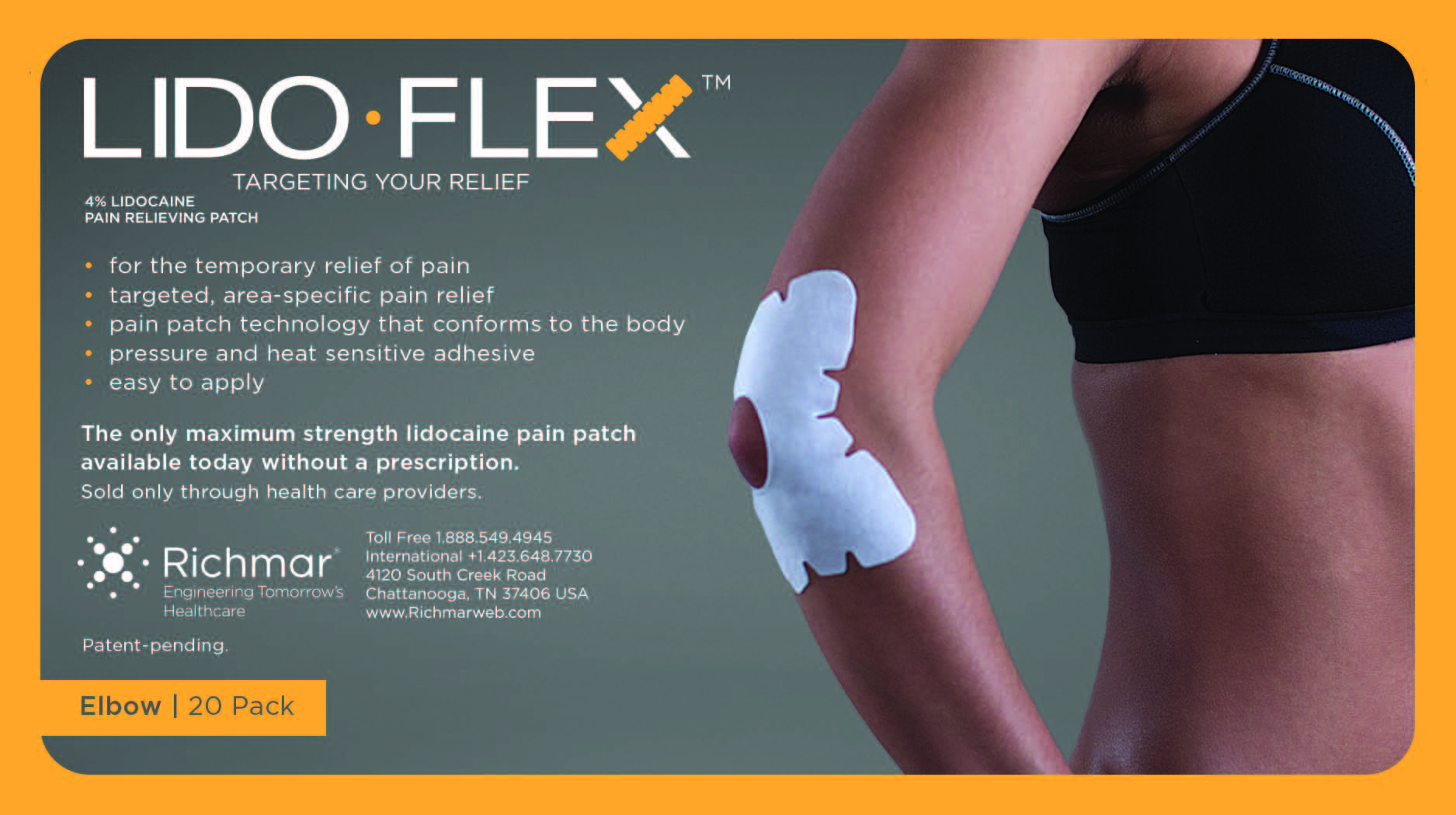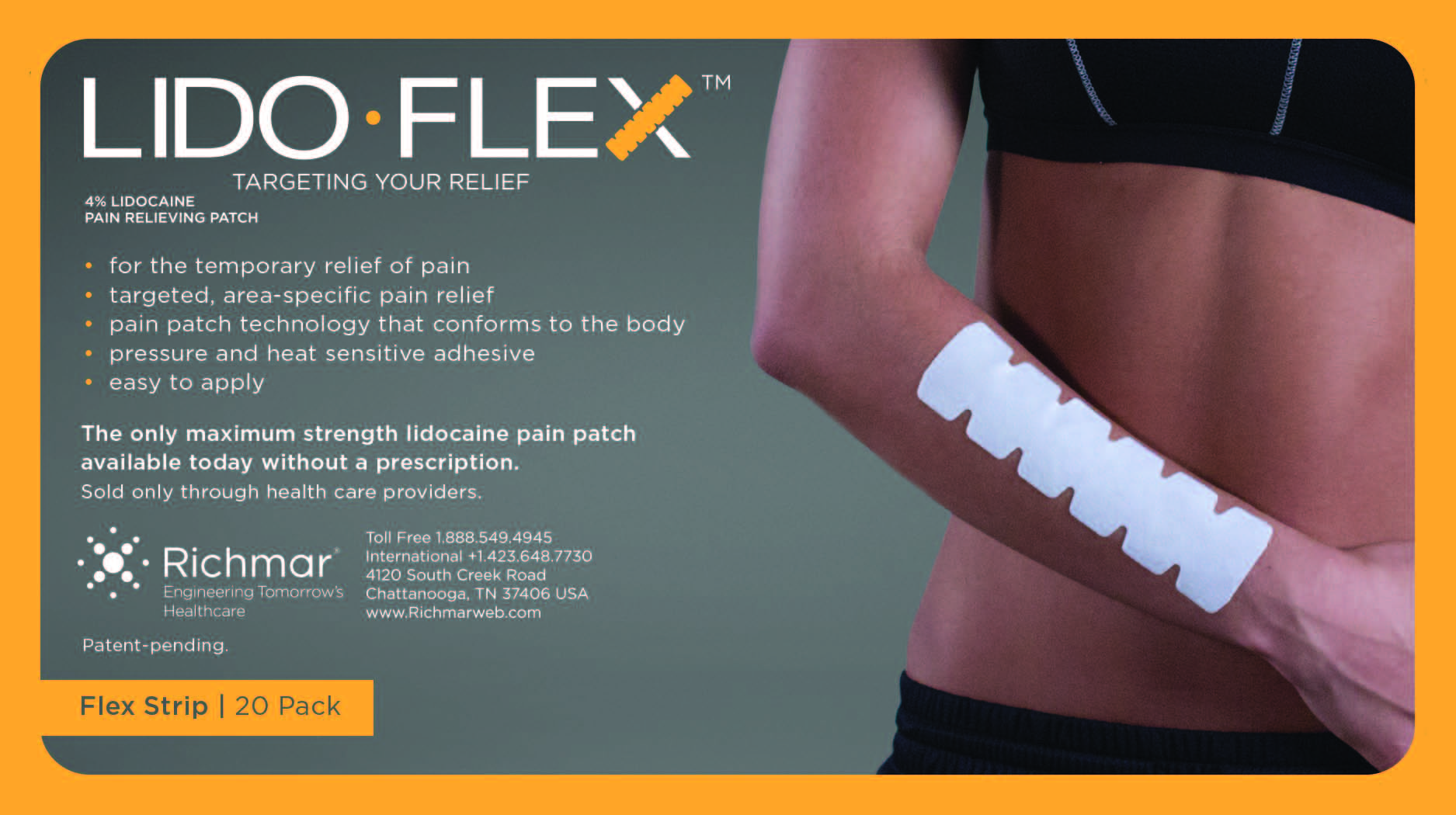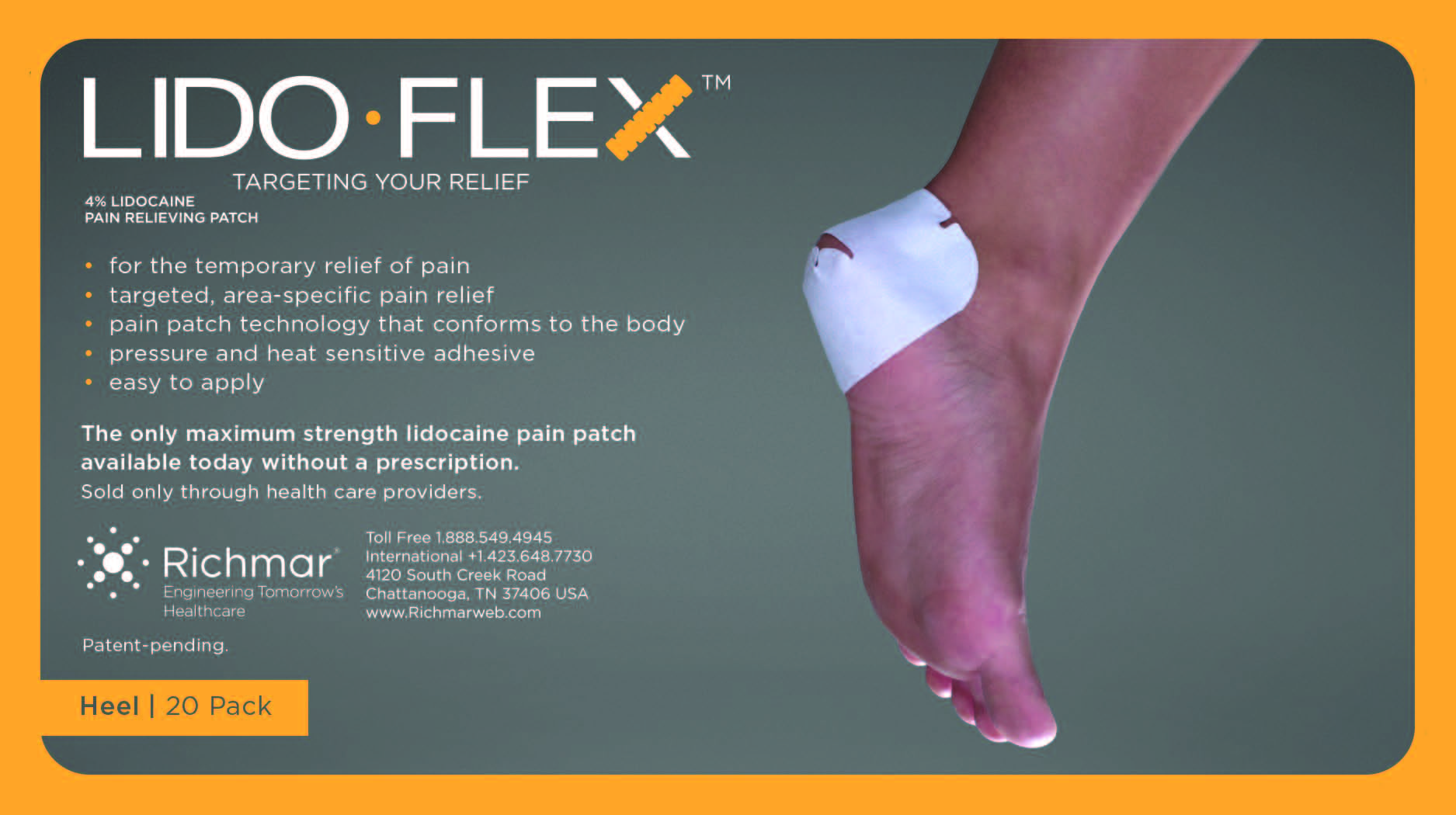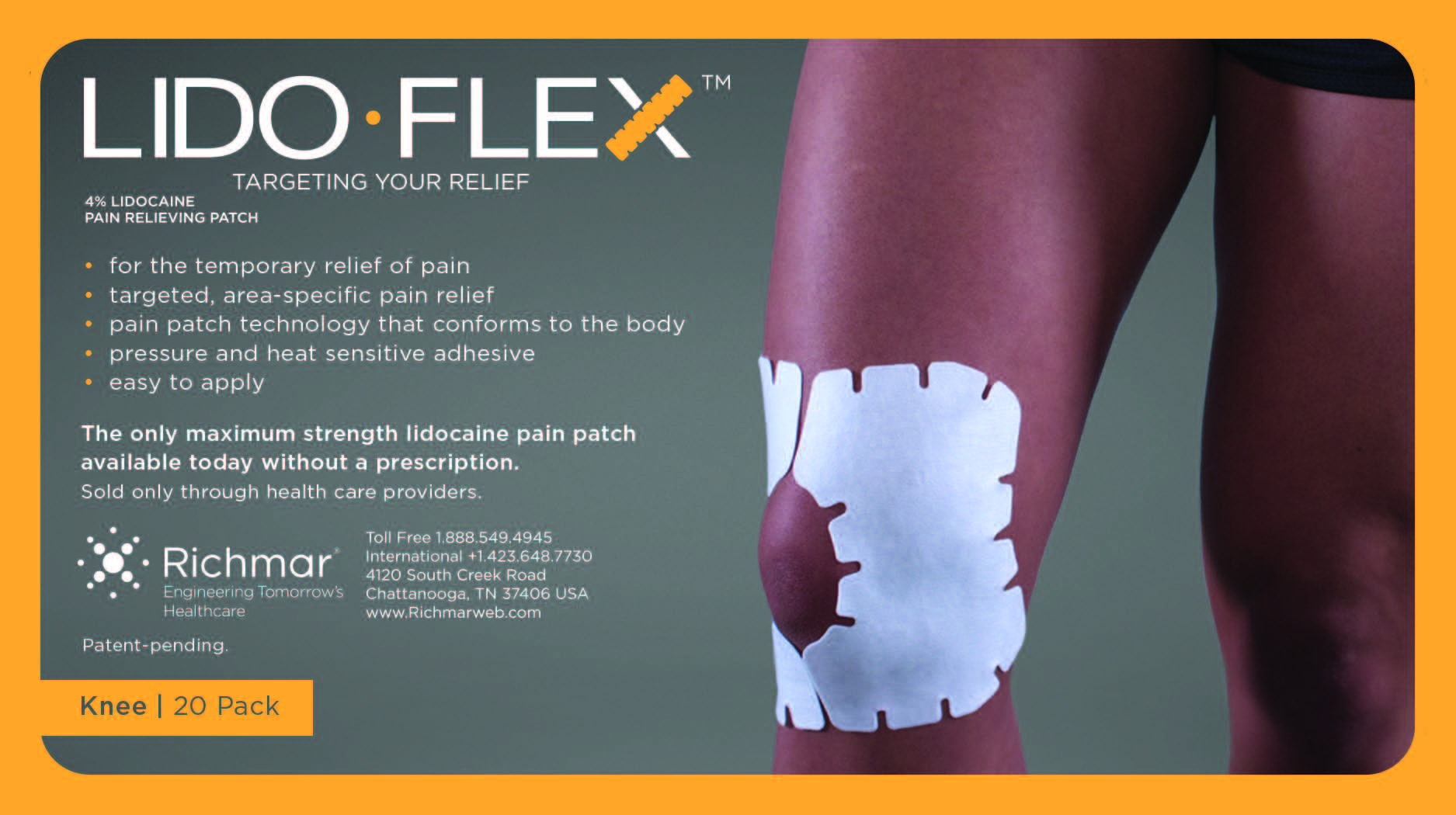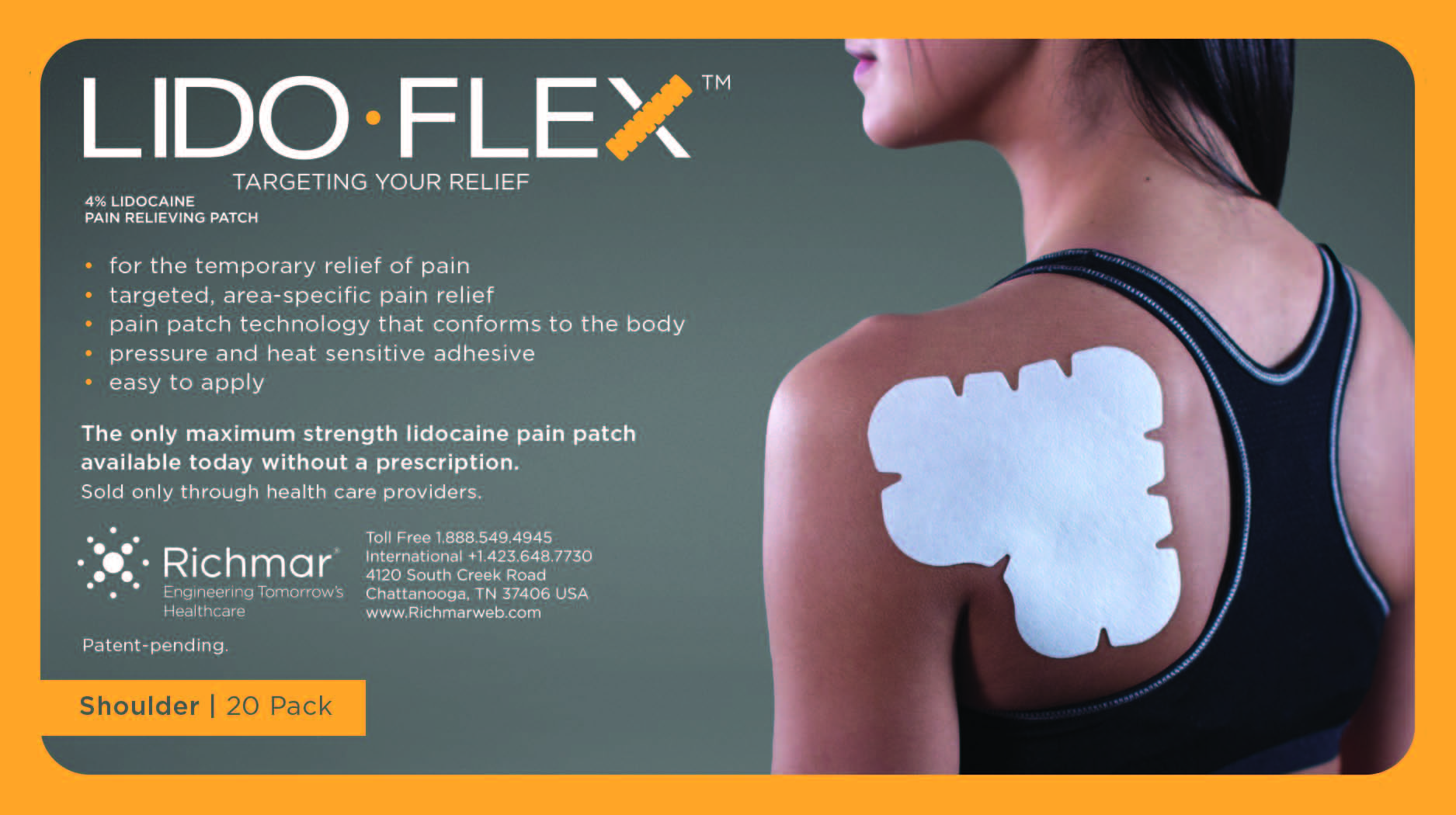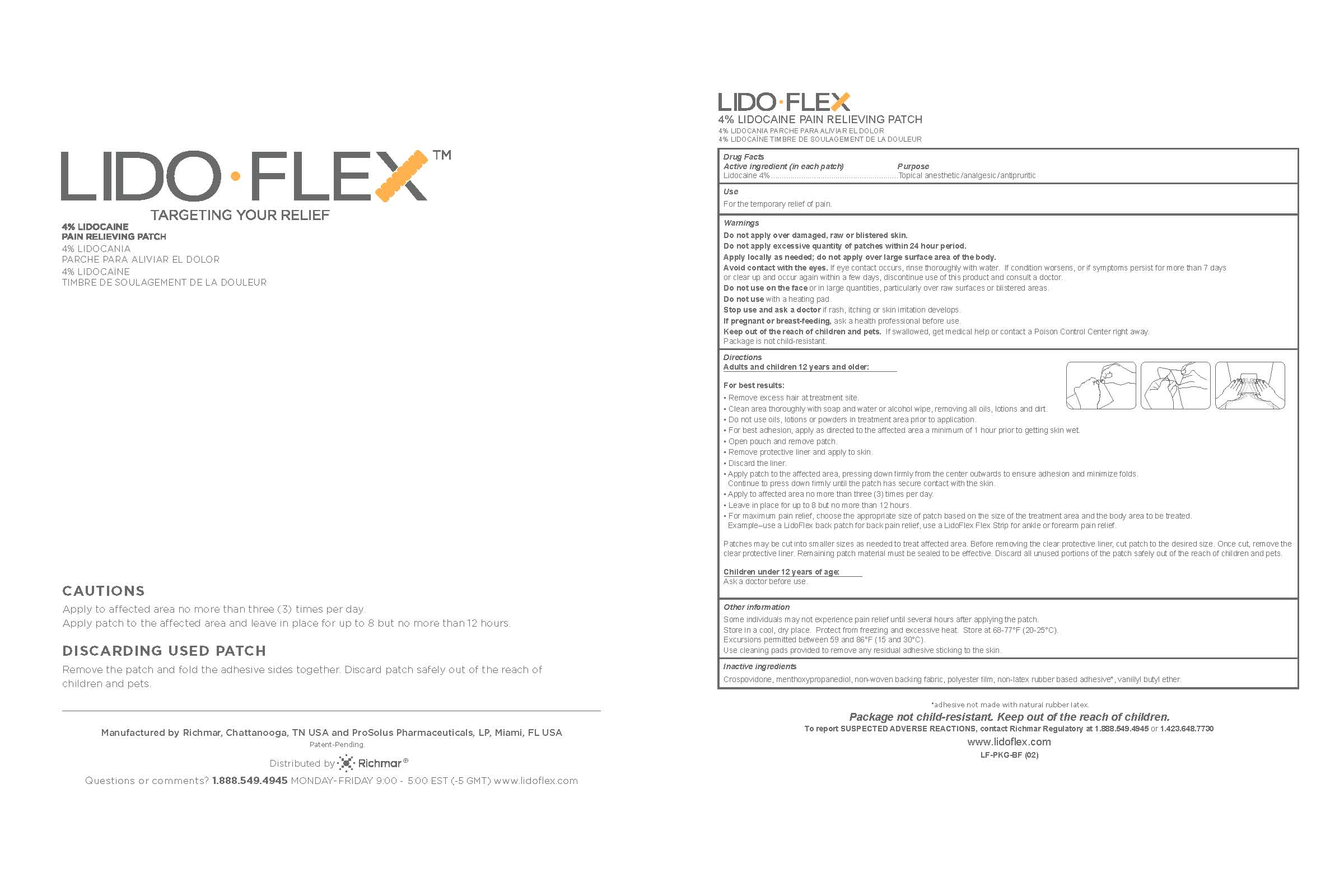 DRUG LABEL: LidoFLEX
NDC: 69313-636 | Form: PATCH
Manufacturer: NAIMCO, INC. DBA RICHMAR, INC.
Category: otc | Type: HUMAN OTC DRUG LABEL
Date: 20161222

ACTIVE INGREDIENTS: LIDOCAINE 25.3 mg/0.24 mg
INACTIVE INGREDIENTS: CROSPOVIDONE; 3-((L-MENTHYL)OXY)PROPANE-1,2-DIOL

LidoFLEX Analgesic/Anesthetic/Antipruritic Patch Products

LIDOCAINE 4% PATCH

4% LIDOCAINE PAIN RELIEVING PATCH
4% LIDOCANIA PARCHE PARA ALIVIAR EL DOLOR
4% LIDOCAÏNE TIMBRE DE SOULAGEMENT DE LA DOULEUR
Drug Facts
Active ingredient (in each patch) Purpose
Lidocaine 4%...........................................................Topical anesthetic/analgesic/antipruritic

Inactive ingredients
Crospovidone, menthoxypropanediol, non-woven backing fabric, polyester film, non-latex rubber based adhesive*, vanillyl butyl ether

*adhesive not made with natural rubber latex.

Warnings

Do not apply over damaged, raw or blistered skin.
Do not apply excessive quantity of patches within 24 hour period.
Apply locally as needed; do not apply over large surface area of the body.
Avoid contact with the eyes. If eye contact occurs, rinse thoroughly with water. If condition worsens, or if symptoms persist for more than 7 days
or clear up and occur again within a few days, discontinue use of this product and consult a doctor.
Do not use on the face or in large quantities, particularly over raw surfaces or blistered areas.
Do not use with a heating pad.
Stop use and ask a doctor if rash, itching or skin irritation develops.
If pregnant or breast-feeding, ask a health professional before use.
Keep out of the reach of children and pets. If swallowed, get medical help or contact a Poison Control Center right away.
Package is not child-resistant.

DOSAGE AND ADMINISTRATION

Apply to affected area no more than three times per day.
Apply patch to the affected area and leave in place for up to 8 but no more than 12 hours.

Inactive Ingredients

Crospovidone, menthoxypropanediol, non-woven backing fabric, polyester film, non-latex rubber based adhesive*, vanillyl butyl ether.

*adhesive not made with natural rubber latex.

Use
For the temporary relief of pain.

KEEP OUT OF REACH OF CHILDREN

Keep out of the reach of children and pets. If swallowed, get medical help or contact a Poison Control Center right away.
Package is not child-resistant.

LidoFLEX 4% Lidocaine Pain Relieving Patch

CAUTIONS

Apply to affected area no more than three (3) times per day.
Apply patch to the affected area and leave in place for up to 8 but no more than 12 hours.
DISCARDING USED PATCH
Remove the patch and fold the adhesive sides together. Discard patch safely out of the reach of
children and pets.
Patent-Pending.
4% LIDOCAINE PAIN RELIEVING PATCH
4% LIDOCANIA PARCHE PARA ALIVIAR EL DOLOR
4% LIDOCAÏNE TIMBRE DE SOULAGEMENT DE LA DOULEUR
Drug Facts
Active ingredient (in each patch) Purpose
Lidocaine 4%...........................................................Topical anesthetic/analgesic/antipruritic
Use
For the temporary relief of pain.
Warnings
Do not apply over damaged, raw or blistered skin.
Do not apply excessive quantity of patches within 24 hour period.
Apply locally as needed; do not apply over large surface area of the body.
Avoid contact with the eyes. If eye contact occurs, rinse thoroughly with water. If condition worsens, or if symptoms persist for more than 7 days
or clear up and occur again within a few days, discontinue use of this product and consult a doctor.
Do not use on the face or in large quantities, particularly over raw surfaces or blistered areas.
Do not use with a heating pad.
Stop use and ask a doctor if rash, itching or skin irritation develops.
If pregnant or breast-feeding, ask a health professional before use.
Keep out of the reach of children and pets. If swallowed, get medical help or contact a Poison Control Center right away.
Package is not child-resistant.
Directions
Adults and children 12 years and older:
For best results:
• Remove excess hair at treatment site.
• Clean area thoroughly with soap and water or alcohol wipe, removing all oils, lotions and dirt.
• Do not use oils, lotions or powders in treatment area prior to application.
• For best adhesion, apply as directed to the affected area a minimum of 1 hour prior to getting skin wet.
• Open pouch and remove patch.
• Remove protective liner and apply to skin.
• Discard the liner.
• Apply patch to the affected area, pressing down firmly from the center outwards to ensure adhesion and minimize folds.
Continue to press down firmly until the patch has secure contact with the skin.
• Apply to affected area no more than three (3) times per day.
• Leave in place for up to 8 but no more than 12 hours.
• For maximum pain relief, choose the appropriate size of patch based on the size of the treatment area and the body area to be treated.
Example–use a LidoFlex back patch for back pain relief, use a LidoFlex Flex Strip for ankle or forearm pain relief.
Patches may be cut into smaller sizes as needed to treat affected area. Before removing the clear protective liner, cut patch to the desired size. Once cut, remove the clear protective liner. Remaining patch material must be sealed to be effective. Discard all unused portions of the patch safely out of the reach of children and pets.
Children under 12 years of age:
Ask a doctor before use.
Other information
Some individuals may not experience pain relief until several hours after applying the patch.
Store in a cool, dry place. Protect from freezing and excessive heat. Store at 68-77°F (20-25°C).
Excursions permitted between 59 and 86°F (15 and 30°C).
Use cleaning pads provided to remove any residual adhesive sticking to the skin.
Inactive ingredients
Crospovidone, menthoxypropanediol, non-woven backing fabric, polyester film, non-latex rubber based adhesive*, vanillyl butyl ether.
*adhesive not made with natural rubber latex.

Package not child-resistant. Keep out of the reach of children.
To report SUSPECTED ADVERSE REACTIONS, contact Richmar Regulatory at 1.888.549.4945 or 1.423.648.7730 www.lidoflex.com